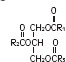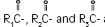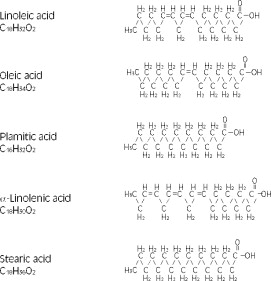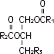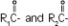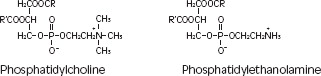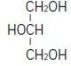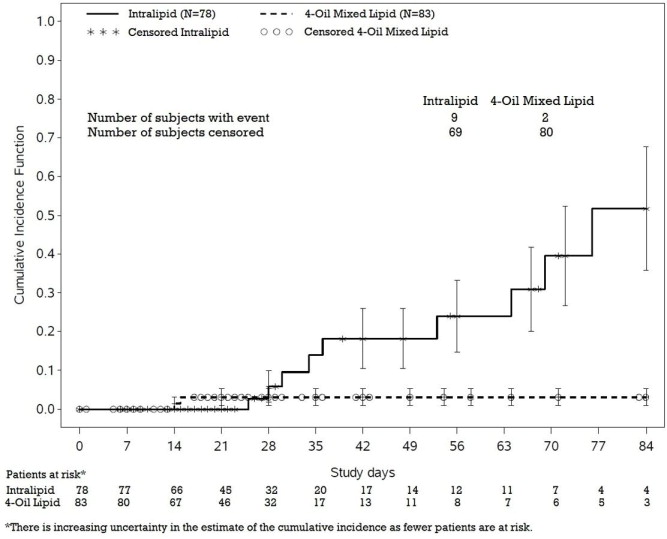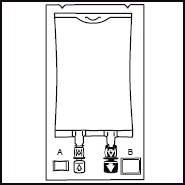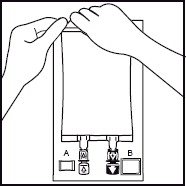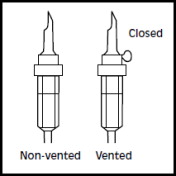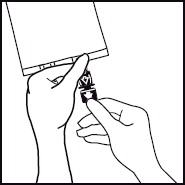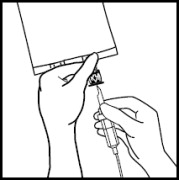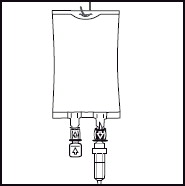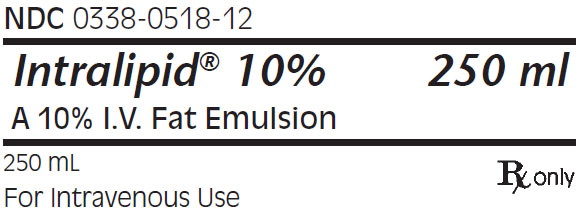 DRUG LABEL: Intralipid

NDC: 0338-0518 | Form: EMULSION
Manufacturer: Baxter Healthcare CORP

Category: prescription | Type: HUMAN PRESCRIPTION DRUG LABEL
Date: 20220725

ACTIVE INGREDIENTS: SOYBEAN OIL
 10 g/100 mL
INACTIVE INGREDIENTS: EGG PHOSPHOLIPIDS; GLYCERIN; SODIUM HYDROXIDE

Intralipid® 10% (A 10% I.V. Fat Emulsion)

DESCRIPTION

Intralipid® 10% (A 10% Intravenous Fat Emulsion) is a sterile, non-pyrogenic fat emulsion prepared for intravenous administration as a source of calories and essential fatty acids. It is made up of 10% Soybean Oil, 1.2% Egg Yolk Phospholipids, 2.25% Glycerin, and Water for Injection. In addition, sodium hydroxide has been added to adjust the pH so that the final product pH is 8. pH range is 6 to 8.9.

The soybean oil is a refined natural product consisting of a mixture of neutral triglycerides of predominantly unsaturated fatty acids with the following structure:

whereare saturated and unsaturated fatty acid residues.

The major component fatty acids are linoleic acid (44-62%), oleic acid (19-30%), palmitic acid (7-14%), α-linolenic acid (4-11%) and stearic acid (1.4-5.5%)^1. These fatty acids have the following chemical and structural formulas:

Purified egg phosphatides are a mixture of naturally occurring phospholipids which are isolated from the egg yolk. These phospholipids have the following general structure:

contain saturated and unsaturated fatty acids that abound in neutral fats. R3 is primarily either the choline or ethanolamine ester of phosphoric acid.

Glycerin is chemically designated C3H8O3 and is a clear colorless, hygroscopic syrupy liquid. It has the following structural formula:

Intralipid 10% (A 10% Intravenous Fat Emulsion) has an osmolality of approximately 300 mOsmol/kg water (which represents 260 mOsmol/L of emulsion) and contains emulsified fat particles of approximately 0.5 micron size.

The total caloric value, including fat, phospholipid and glycerin, is 1.1 kcal per mL of Intralipid 10%. The phospholipids present contribute 47 milligrams or approximately 1.5 mmol of phosphorus per 100 mL of the emulsion.

The primary plastic container (BiofineTM) is made from multilayered film specifically designed for parenteral nutrition drug products. The film is polypropylene based comprising three co-extruded layers. It contains no plasticizers and exhibits virtually no leachables. The container does not contain DEHP (di(2-ethylhexyl) phthalate), PVC. The container is nontoxic and biologically inert. This product is not made with natural rubber latex.

The container-emulsion unit is a closed system and is not dependent upon entry of external air during administration.

The container is overwrapped to provide protection from the physical environment and to provide an additional moisture barrier when necessary.

CLINICAL PHARMACOLOGY

Intralipid 10% is metabolized and utilized as a source of energy causing an increase in heat production, decrease in respiratory quotient and increase in oxygen consumption. The infused fat particles are cleared from the blood stream in a manner thought to be comparable to the clearing of chylomicrons.

Intralipid 10% will prevent the biochemical lesions of essential fatty acid deficiency (EFAD) and correct the clinical manifestations of the EFAD syndrome.

INDICATIONS AND USAGE

Intralipid® 10% is indicated as a source of calories and essential fatty acids for patients requiring parenteral nutrition for extended periods of time (usually for more than 5 days) and as a source of essential fatty acids for prevention of EFAD.

CONTRAINDICATIONS

Intralipid 10% is contraindicated in patients with:

- Disturbances of normal fat metabolism such as pathologic hyperlipemia, lipoid nephrosis or acute pancreatitis if accompanied by hyperlipidemia.
- Known hypersensitivity to egg, soybean, peanut protein, or to any of the active ingredients or excipients of Intralipid 10%.

WARNINGS

Deaths in preterm infants after infusion of intravenous fat emulsion have been reported in the medical literature^2.

Autopsy findings included intravascular fat accumulation in the lungs. Treatment of premature and low birth weight infants with intravenous fat emulsion must be based upon careful benefit-risk assessment. Strict adherence to the recommended total daily dose is mandatory; hourly infusion rate should be as slow as possible in each case and should not in any case exceed 1 g fat/kg in four hours. Premature and small for gestational age infants have poor clearance of intravenous fat emulsion and increased free fatty acid plasma levels following fat emulsion infusion; therefore, serious consideration must be given to administration of less than the maximum recommended doses in these patients in order to decrease the likelihood of intravenous fat overload. The infant's ability to eliminate the infused fat from the circulation must be carefully monitored (such as serum triglycerides and/or plasma free fatty acid levels).

The lipemia must clear between daily infusions.

Caution should be exercised in administering of Intralipid 10% (A 10% Intravenous Fat Emulsion) to patients with severe liver damage, pulmonary disease, anemia or blood coagulation disorders, or when there is danger of fat embolism.

Parenteral Nutrition-Associated Liver Disease and Other Hepatobiliary Disorders

Risk of Parenteral Nutrition-Associated Liver Disease

Parenteral nutrition-associated liver disease (PNALD), also referred to as intestinal failure- associated liver disease (IFALD), can present as cholestasis or hepatic steatosis, and may progress to steatohepatitis with fibrosis and cirrhosis (possibly leading to chronic hepatic failure). The etiology of PNALD is multifactorial; however, intravenously administered phytosterols (plant sterols) contained in plant-derived lipid emulsions, including Intralipid, have been associated with development of PNALD.

In a randomized active-controlled, double-blind, parallel-group, multi-center study that included 152 neonates and 9 patients ranging in age from 29 to 153 days who were expected to require PN for at least 28 days, parenteral nutrition-associated cholestasis (PNAC), a precursor to PNALD, developed more frequently in Intralipid-treated patients than in patients treated with a 4-oil mixed lipid emulsion.

PNAC (defined as direct bilirubin >2mg/dl with a second confirmed elevation >2mg/dl at least 7 days later) occurred in 11.5% (9/78) in Intralipid-treated patients and 2.4% (2/83) of patients treated with a 4-oil mixed lipid emulsion. Most PNAC events occurred in patients who were treated for longer than 28 days.

The estimated cumulative incidence of PNAC is shown in the Kaplan-Meier cumulative incidence curve in Figure 1.

Figure 1: Cumulative Incidence Curve of Time to Parenteral Nutrition-Associated Cholestasis (PNAC) with Standard Error Bars

Monitor liver tests in patients treated with Intralipid and consider discontinuation or dosage reduction if abnormalities occur.

Other Hepatobiliary Disorders

Hepatobiliary disorders including cholecystitis and cholelithiasis have developed in some PN-treated patients without preexisting liver disease.

Monitor liver tests when administering Intralipid. Patients developing signs of hepatobiliary disorders should be assessed early to determine whether these conditions are related to Intralipid use.

Aluminum Toxicity

This product contains aluminum that may be toxic. Aluminum may reach toxic levels with prolonged parenteral administration if kidney function is impaired. Premature neonates are particularly at risk because their kidneys are immature, and they require large amounts of calcium and phosphate solutions, which contain aluminum.

Research indicates that patients with impaired kidney function, including premature neonates, who receive parenteral levels of aluminum at greater than 4 to 5 mcg/kg/day accumulate aluminum at levels associated with central nervous system and bone toxicity. Tissue loading may occur at even lower rates of administration.

PRECAUTIONS

When Intralipid 10% is administered, the patient's capacity to eliminate the infused fat from the circulation must be monitored by use of an appropriate laboratory determination of serum triglycerides. Overdosage must be avoided.

During intravenous administration with Intralipid 10%, perform liver tests to monitor for PNALD. If patients develop liver test abnormalities, consider discontinuation of Intralipid or dosage reduction. (See WARNINGS section)

Frequent platelet counts should be done in neonatal patients receiving parenteral nutrition with Intralipid 10%.

Drug product contains no more than 25 mcg/L of aluminum.

Carcinogenesis, Mutagenesis, Impairment of Fertility:

Studies with Intralipid have not been performed to evaluate carcinogenic potential, mutagenic potential, or effects on fertility.

PREGNANCY

Pregnancy: Animal reproduction studies have not been conducted with Intralipid. It is also not known whether Intralipid can cause fetal harm when administered to a pregnant woman or can affect reproduction capacity. Intralipid should be given to a pregnant woman only if clearly needed.

NURSING MOTHERS

Nursing Mothers: Caution should be exercised when Intralipid is administered to a nursing woman.

Pediatric Use: See DOSAGE AND ADMINISTRATION.

ADVERSE REACTIONS

The adverse reactions observed can be separated into two classes:

1. Those more frequently encountered are due: either to contamination of the intravenous catheter and result in sepsis, or to vein irritation by concurrently infused hypertonic solutions and may result in thrombophlebitis. These adverse reactions are inseparable from the hyperalimentation procedure with or without Intralipid 10% (A 10% I.V. Fat Emulsion).
2. Less frequent reactions more directly related to Intralipid 10% are: a) immediate or early adverse reactions, each of which has been reported to occur in clinical trials, in an incidence of less than 1%; dyspnea, cyanosis, allergic reactions, hyperlipemia, hypercoagulability, nausea, vomiting, headache, flushing, increase in temperature, sweating, sleepiness, pain in the chest and back, slight pressure over the eyes, dizziness, and irritation at the site of infusion, and, rarely, thrombocytopenia in neonates; b) delayed adverse reactions such as hepatomegaly, jaundice due to central lobular cholestasis, splenomegaly, thrombocytopenia, leukopenia, transient increases in liver tests, and overloading syndrome (focal seizures, fever, leukocytosis, hepatomegaly, splenomegaly and shock).

The deposition of a brown pigmentation in the reticuloendothelial system, the so-called “intravenous fat pigment,” has been reported in patients infused with Intralipid 10%. The causes and significance of this phenomenon are unknown.

OVERDOSAGE

In the event of fat overload during therapy, stop the infusion of Intralipid 10% until visual inspection of the plasma, determination of triglyceride concentrations, or measurement of plasma light-scattering activity by nephelometry indicates the lipid has cleared. Re- evaluate the patient and institute appropriate corrective measures. See WARNINGS and PRECAUTIONS.

DOSAGE AND ADMINISTRATION

Intralipid 10% should be administered as a part of Intravenous nutrition via peripheral vein or by central venous infusion.

Adult Patients

The initial rate of infusion in adults should be 1 mL/minute for the first 15 to 30 minutes of infusion. If no untoward reactions occur (see ADVERSE REACTIONS section), the infusion rate can be increased to 2 mL/minute. Not more than 500 mL of Intralipid 10% (A 10% I.V. Fat Emulsion) should be infused into adults on the first day of therapy. If the patient has no untoward reactions, the dose can be increased on the following day. The daily dosage should not exceed 2.5 g of fat/kg of body weight (25 mL of Intralipid 10% per kg). Intralipid 10% should make up no more than 60% of the total caloric input to the patient. Maximum infusion rate should not exceed 0.1 g/kg/hr.

Carbohydrate and a source of amino acids should comprise the remaining caloric input.

Pediatric Patients

The dosage for premature infants starts at 0.5 g fat/kg body weight/24 hours (5 mL Intralipid 10%) and may be increased in relation to the infant's ability to eliminate fat. The maximum recommended dosage is 3 g fat/kg/24 hours.

Pediatric patients may be at risk for parenteral nutrition-associated liver disease (PNALD), also known as intestinal failure-associated liver disease (see WARNINGS section) when receiving Intralipid for durations exceeding two weeks. During intravenous administration of Intralipid 10%, perform liver tests to monitor for PNALD.

The initial rate of infusion in older pediatric patients should be no more than 0.1 mL/minute for the first 10 to 15 minutes. If no untoward reactions occur, the rate can be changed to permit infusion of 1 mL of Intralipid 10%/kg/hour (equivalent to 0.1 g/kg/hour). The daily dosage should not exceed 3 g of fat/kg of body weight^3. Intralipid 10% (equivalent to 0.125 g/kg/hour) should make up no more than 60% of the total caloric input to the patient. Carbohydrate and a source of amino acids should comprise the remaining caloric input.

Essential Fatty Acid Deficiency

When Intralipid 10% (A 10% I.V. Fat Emulsion) is administered to correct essential fatty acid deficiency, eight to ten percent of the caloric input should be supplied by Intralipid 10% in order to provide adequate amounts of linoleic and linolenic acids. When EFAD occurs together with stress, the amount of Intralipid 10% needed to correct the deficiency may be increased.

Administration

See MIXING GUIDELINES AND LIMITATIONS section for information regarding mixing this fat emulsion with other parenteral fluids.

Intralipid 10% can be infused into the same central or peripheral vein as carbohydrate/amino acids solutions by means of a Y-connector near the infusion site. This allows for mixing of the emulsion immediately before entering the vein or for alternation of each parenteral fluid. If infusion pumps are used, flow rates of each parenteral fluid should be controlled with a separate pump. Fat emulsion may also be infused through a separate peripheral site. Use a 1.2 micron filter with Intralipid 10%. Filters of less than 1.2 micron pore size must not be used. Conventional administration sets and TPN pooling bags contain polyvinyl chloride (PVC) components that have DEHP (di(2-ethylhexyl) phthalate) as a plasticizer. Fat‑containing fluids such as Intralipid 10% extract DEHP from these PVC components and it may be advisable to consider infusion of Intralipid 10% through a non-DEHP administration set. Do not use any bag in which there appears to be an oiling out on the surface of the emulsion. Parenteral drug products should be inspected visually for particulate matter and discoloration prior to administration whenever solution and container permit.

MIXING GUIDELINES AND LIMITATIONS

Intralipid 10% (A 10% I.V. Fat Emulsion) may be mixed with Amino Acid and Dextrose Injections where compatibility have been demonstrated. Additives known to be incompatible should not be used. Please consult with pharmacist. If, in the informed judgment of the physician, it is deemed advisable to introduce additives, use aseptic technique. Mix thoroughly when additives have been introduced. Do not store solutions containing additives (e.g., Vitamins and Minerals).

Protect the admixed PN solution from light.

When being mixed the following proper mixing sequence must be followed to minimize pH related problems by ensuring that typically acidic Dextrose Injections are not mixed with lipid emulsions alone:

1. Transfer Dextrose Injection to the TPN Admixture Container
2. Transfer Amino Acid Injection
3. Transfer Intralipid 10% (A 10% Intravenous Fat Emulsion)

Note: Amino Acid Injection, Dextrose Injection and Intralipid 10% may be simultaneously transferred to the admixture container. Admixing should be accompanied by gentle agitation to avoid localized concentration effects.

Additives must not be added directly to Intralipid 10% and in no case should Intralipid 10% be added to the TPN container first. Bags should be shaken gently after each addition to minimize localized concentration.

If the admixture is not used immediately, the in-use storage time and conditions prior to use are the responsibility of the user and should normally not be longer than 24 hours at 2-8°C. After removal from storage at 2-8°C, the admixture should be infused within 24 hours.

It is essential that the admixture be prepared using strict aseptic techniques as this nutrient mixture is a good growth medium for microorganisms.

Supplemental electrolytes, trace metals or multivitamins may be required in accordance with the prescription of the attending physician.

The prime destabilizers of emulsions are excessive acidity (low pH) and inappropriate electrolyte content. Careful consideration should be given to additions of divalent cations (Ca^++ and Mg^++) which have been shown to cause emulsion instability. Amino acid solutions exert a buffering effect protecting the emulsion. The admixture should be inspected carefully for “breaking or oiling out” of the emulsion. “Breaking or oiling out” is described as the separation of the emulsion and can be visibly identified by a yellowish streaking or the accumulation of yellowish droplets in the admixed emulsion. The admixture should also be examined for particulates. The admixture must be discarded if any of the above is observed.

HOW SUPPLIED

Intralipid 10% is supplied as a sterile emulsion in the following fill sizes: 100 mL, 250 mL and 500 mL.

100 mL: 0338-0518-58

250 mL: 0338-0518-12

500 mL: 0338-0518-13

STORAGE

Intralipid 10% should not be stored above 25°C (77°F). Do not freeze Intralipid 10%. If accidentally frozen, discard the bag.

REFERENCES

1. Padley FB: “Major Vegetable Fats”, The Lipid Handbook (Gunstone FD, Harwood JL, Padley FB, eds.), Chapman and Hall Ltd., Cambridge, UK (1986), pp. 88-9.
2. Levene MI, Wigglesworth JS, Desai R: Pulmonary fat accumulation after Intralipid infusion in the preterm infant. Lancet 1980; 2(8199):815-8.
3. American Academy of Pediatrics: Use of intravenous fat emulsion in pediatric patients. Pediatrics 1981; 68:5(Nov) 738-43.

(Rev May 2022) Manufactured for
Baxter Healthcare Corporation
Deerfield, IL 60015 USA

Manufactured by:
Fresenius Kabi,
Uppsala, Sweden

Intralipid® is a registered trademark of Fresenius Kabi AB.

Instruction for Use - Intralipid® 10% Container

1.

1. The integrity indicator (Oxalert™) A should be inspected before removing the overwrap. If the indicator is black the overwrap is damaged and the product should be discarded.

2.

2. Remove the overwrap by tearing at the notch and pulling down along the container. The Oxalert sachet (A) and the oxygen absorber (B) should be discarded. Place the bag on a clean, flat surface or hang on a support hook.

3.

3. Use a non-vented infusion set or close the air vent on a vented set. Follow the instructions for use for the infusion set. Use a spike with diameter of 5.6 +/- 0.1 mm.
Use a 1.2 micron filter as part of the infusion set. Filters of less than 1.2 micron pore size must not be used.

4.

4. Break off the tamper-evident arrow flag from the blue infusion port.

5.

5. Hold the base of the infusion port firmly and insert the spike straight through the center of the septum by rotating the wrist slightly if needed.
NOTE: Assure that the spike is inserted straight into the port and not at an angle.
Inspect the bag and contents for particulate matter in a well-lit environment prior to administration. Discard the bag if there are any signs of discoloration or particulates.

6.

6. Hang the bag in the hanger cut and start infusion.

PACKAGE LABEL

PACKAGE LABEL - PRINCIPAL DISPLAY - Intralipid 250 mL Container Label

NDC 0338-0518-12

Intralipid ® 1 0%

A 10% I.V. Fat Emulsion

250 mL
For Intravenous Use

Rx only